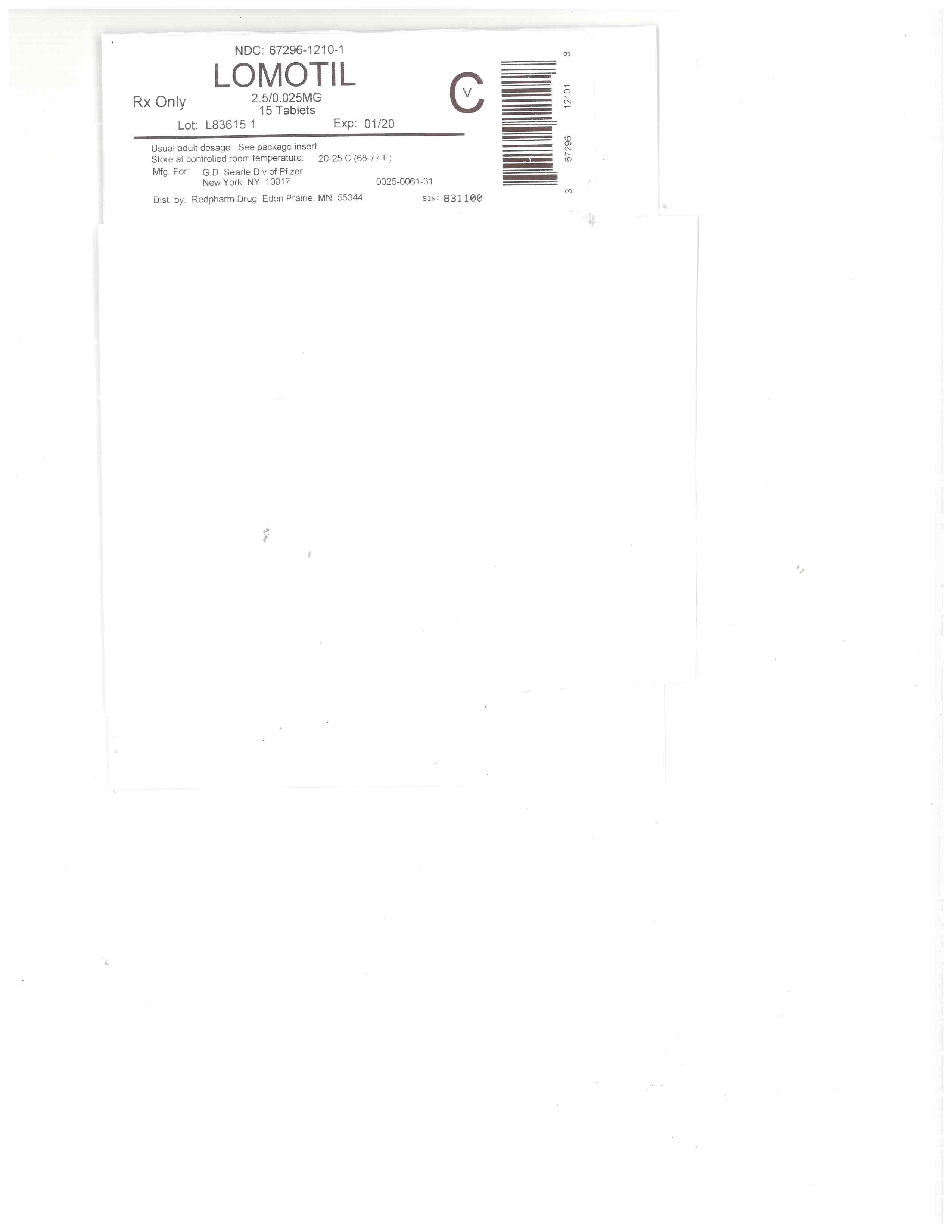 DRUG LABEL: Lomotil
NDC: 67296-1210 | Form: TABLET
Manufacturer: RedPharm Drug, Inc.
Category: prescription | Type: HUMAN PRESCRIPTION DRUG LABEL
Date: 20220120
DEA Schedule: CV

ACTIVE INGREDIENTS: ATROPINE SULFATE 0.025 mg/1 1; DIPHENOXYLATE HYDROCHLORIDE 2.5 mg/1 1
INACTIVE INGREDIENTS: ACACIA; SORBITOL; SUCROSE; STARCH, CORN; MAGNESIUM STEARATE; TALC

DESCRIPTION

Each Lomotil tablet and each 5 ml of Lomotil liquid for oral use contains:

diphenoxylate hydrochloride 2.5 mg

atropine sulfate ................. 0.025 mg

Diphenoxylate hydrochloride, an antidiarrheal, is ethyl 1-(3-cyano-3,3-diphenylpropyl)-4-phenylisonipecotate monohydrochloride and has the following structural formula:

[Chemical Structure]

Atropine sulfate, an anticholinergic, is endo-(±)-α-(hydroxymethyl) benzeneacetic acid 8-methyl-8-azabicyclo[3.2.1] oct-3-yl ester sulfate (2:1) (salt) monohydrate and has the following structural formula:

[Chemical Structure]

A subtherapeutic amount of atropine sulfate is present to discourage deliberate overdosage.

Inactive ingredients of Lomotil tablets include acacia, corn starch, magnesium stearate, sorbitol, sucrose, and talc. Inactive ingredients of Lomotil liquid include cherry flavor, citric acid, ethyl alcohol 15%, FD&C Yellow No. 6, glycerin, sodium phosphate, sorbitol, and water.

CLINICAL PHARMACOLOGY

Diphenoxylate is rapidly and extensively metabolized in man by ester hydrolysis to diphenoxylic acid (difenoxine), which is biologically active and the major metabolite in the blood. After a 5-mg oral dose of carbon-14 labeled diphenoxylate hydrochloride in ethanolic solution was given to three healthy volunteers, an average of 14% of the drug plus its metabolites was excreted in the urine and 49% in the feces over a four-day period. Urinary excretion of the unmetabolized drug constituted less than 1% of the dose, and diphenoxylic acid plus its glucuronide conjugate constituted about 6% of the dose. In a 16-subject crossover bioavailability study, a linear relationship in the dose range of 2.5 to 10 mg was found between the dose of diphenoxylate hydrochloride (given as Lomotil liquid) and the peak plasma concentration, the area under the plasma concentration-time curve, and the amount of diphenoxylic acid excreted in the urine. In the same study the bioavailability of the tablet compared with an equal dose of the liquid was approximately 90%. The average peak plasma concentration of diphenoxylic acid following ingestion of four 2.5-mg tablets was 163 ng/ml at about 2 hours, and the elimination half-life of diphenoxylic acid was approximately 12 to 14 hours.

In dogs, diphenoxylate hydrochloride has a direct effect on circular smooth muscle of the bowel that conceivably results in segmentation and prolongation of gastrointestinal transit time. The clinical antidiarrheal action of diphenoxylate hydrochloride may thus be a consequence of enhanced segmentation that allows increased contact of the intraluminal contents with the intestinal mucosa.

INDICATIONS AND USAGE

Lomotil is effective as adjunctive therapy in the management of diarrhea.

CONTRAINDICATIONS

Lomotil is contraindicated in patients with

Known hypersensitivity to diphenoxylate or atropine.
Obstructive jaundice.
Diarrhea associated with pseudomembranous enterocolitis or enterotoxin-producing bacteria.

WARNINGS

LOMOTIL IS NOT AN INNOCUOUS DRUG AND DOSAGE RECOMMENDATIONS SHOULD BE STRICTLY ADHERED TO, ESPECIALLY IN CHILDREN. LOMOTIL IS NOT RECOMMENDED FOR CHILDREN UNDER 2 YEARS OF AGE. OVERDOSAGE MAY RESULT IN SEVERE RESPIRATORY DEPRESSION AND COMA, POSSIBLY LEADING TO PERMANENT BRAIN DAMAGE OR DEATH (SEE OVERDOSAGE). THEREFORE, KEEP THIS MEDICATION OUT OF THE REACH OF CHILDREN.

THE USE OF LOMOTIL SHOULD BE ACCOMPANIED BY APPROPRIATE FLUID AND ELECTROLYTE THERAPY, WHEN INDICATED. IF SEVERE DEHYDRATION OR ELECTROLYTE IMBALANCE IS PRESENT, LOMOTIL SHOULD BE WITHHELD UNTIL APPROPRIATE CORRECTIVE THERAPY HAS BEEN INITIATED. DRUG-INDUCED INHIBITION OF PERISTALSIS MAY RESULT IN FLUID RETENTION IN THE INTESTINE, WHICH MAY FURTHER AGGRAVATE DEHYDRATION AND ELECTROLYTE IMBALANCE.

LOMOTIL SHOULD BE USED WITH SPECIAL CAUTION IN YOUNG CHILDREN BECAUSE THIS AGE GROUP MAY BE PREDISPOSED TO DELAYED DIPHENOXYLATE TOXICITY AND BECAUSE OF THE GREATER VARIABILITY OF RESPONSE IN THIS AGE GROUP.

Antiperistaltic agents may prolong and/or worsen diarrhea associated with organisms that penetrate the intestinal mucosa (toxigenic E. coli, Salmonella, Shigella), and pseudomembranous enterocolitis associated with broad-spectrum antibiotics. Antiperistaltic agents should not be used in these conditions.

In some patients with acute ulcerative colitis, agents that inhibit intestinal motility or prolong intestinal transit time have been reported to induce toxic megacolon. Consequently, patients with acute ulcerative colitis should be carefully observed and Lomotil therapy should be discontinued promptly if abdominal distention occurs or if other untoward symptoms develop.

Since the chemical structure of diphenoxylate hydrochloride is similar to that of meperidine hydrochloride, the concurrent use of Lomotil with monoamine oxidase (MAO) inhibitors may, in theory, precipitate hypertensive crisis.

Lomotil should be used with extreme caution in patients with advanced hepatorenal disease and in all patients with abnormal liver function since hepatic coma may be precipitated.

Diphenoxylate hydrochloride may potentiate the action of barbiturates, tranquilizers, and alcohol. Therefore, the patient should be closely observed when any of these are used concomitantly.

PRECAUTIONS

General

Since a subtherapeutic dose of atropine has been added to the diphenoxylate hydrochloride, consideration should be given to the precautions relating to the use of atropine. In children, Lomotil should be used with caution since signs of atropinism may occur even with recommended doses, particularly in patients with Down's syndrome.

Information For Patients

INFORM THE PATIENT (PARENT OR GUARDIAN) NOT TO EXCEED THE RECOMMENDED DOSAGE AND TO KEEP LOMOTIL OUT OF THE REACH OF CHILDREN AND IN A CHILD-RESISTANT CONTAINER. INFORM THE PATIENT OF THE CONSEQUENCES OF OVERDOSAGE, INCLUDING SEVERE RESPIRATORY DEPRESSION AND COMA, POSSIBLY LEADING TO PERMANENT BRAIN DAMAGE OR DEATH. Lomotil may produce drowsiness or dizziness. The patient should be cautioned regarding activities requiring mental alertness, such as driving or operating dangerous machinery. Potentiation of the action of alcohol, barbiturates, and tranquilizers with concomitant use of Lomotil should be explained to the patient. The physician should also provide the patient with other information in this labeling, as appropriate.

Drug Interactions

Known drug interactions include barbiturates, tranquilizers, and alcohol. Lomotil may interact with MAO inhibitors (see WARNINGS).

In studies with male rats, diphenoxylate hydrochloride was found to inhibit the hepatic microsomal enzyme system at a dose of 2 mg/kg/day. Therefore, diphenoxylate has the potential to prolong the biological half-lives of drugs for which the rate of elimination is dependent on the microsomal drug metabolizing enzyme system.

Carcinogenesis, Mutagenesis, Impairment Of Fertility

No long-term study in animals has been performed to evaluate carcinogenic potential. Diphenoxylate hydrochloride was administered to male and female rats in their diets to provide dose levels of 4 and 20 mg/kg/day throughout a three-litter reproduction study. At 50 times the human dose (20 mg/kg/day), female weight gain was reduced and there was a marked effect on fertility as only 4 of 27 females became pregnant in three test breedings. The relevance of this finding to usage of Lomotil in humans is unknown.

Pregnancy

Pregnancy Category C. Diphenoxylate hydrochloride has been shown to have an effect on fertility in rats when given in doses 50 times the human dose (see above discussion). Other findings in this study include a decrease in maternal weight gain of 30% at 20 mg/kg/day and of 10% at 4 mg/kg/day. At 10 times the human dose (4 mg/kg/day), average litter size was slightly reduced.

Teratology studies were conducted in rats, rabbits, and mice with diphenoxylate hydrochloride at oral doses of 0.4 to 20 mg/kg/day. Due to experimental design and small numbers of litters, embryotoxic, fetotoxic, or teratogenic effects cannot be adequately assessed. However, examination of the available fetuses did not reveal any indication of teratogenicity.

There are no adequate and well-controlled studies in pregnant women. Lomotil should be used during pregnancy only if the anticipated benefit justifies the potential risk to the fetus.

Nursing Mothers

Caution should be exercised when Lomotil is administered to a nursing woman, since the physicochemical characteristics of the major metabolite, diphenoxylic acid, are such that it may be excreted in breast milk and since it is known that atropine is excreted in breast milk.

Pediatric Use

Lomotil may be used as an adjunct to the treatment of diarrhea but should be accompanied by appropriate fluid and electrolyte therapy, if needed. LOMOTIL IS NOT RECOMMENDED FOR CHILDREN UNDER 2 YEARS OF AGE. Lomotil should be used with special caution in young children because of the greater variability of response in this age group. SeeWARNINGS and DOSAGE AND ADMINISTRATION. In case of accidental ingestion by children, see OVERDOSAGE for recommended treatment.

ADVERSE REACTIONS

At therapeutic doses, the following have been reported; they are listed in decreasing order of severity, but not of frequency:

Nervous system: numbness of extremities, euphoria, depression, malaise/lethargy, confusion, sedation/drowsiness, dizziness, restlessness, headache.

Allergic: anaphylaxis, angioneurotic edema, urticaria, swelling of the gums, pruritus.

Gastrointestinal system: toxic megacolon, paralytic ileus, pancreatitis, vomiting, nausea, anorexia, abdominal discomfort.

The following atropine sulfate effects are listed in decreasing order of severity, but not of frequency: hyperthermia, tachycardia, urinary retention, flushing, dryness of the skin and mucous membranes. These effects may occur, especially in children.

THIS MEDICATION SHOULD BE KEPT IN A CHILD-RESISTANT CONTAINER AND OUT OF THE REACH OF CHILDREN SINCE AN OVERDOSAGE MAY RESULT IN SEVERE RESPIRATORY DEPRESSION AND COMA, POSSIBLY LEADING TO PERMANENT BRAIN DAMAGE OR DEATH.

DRUG ABUSE AND DEPENDENCE

Controlled Substance

Lomotil is classified as a Schedule V controlled substance by federal regulation. Diphenoxylate hydrochloride is chemically related to the narcotic analgesic meperidine.

Drug abuse and dependence

In doses used for the treatment of diarrhea, whether acute or chronic, diphenoxylate has not produced addiction.

Diphenoxylate hydrochloride is devoid of morphine-like subjective effects at therapeutic doses. At high doses it exhibits codeine-like subjective effects. The dose which produces antidiarrheal action is widely separated from the dose which causes central nervous system effects. The insolubility of diphenoxylate hydrochloride in commonly available aqueous media precludes intravenous self-administration. A dose of 100 to 300 mg/day, which is equivalent to 40 to 120 tablets, administered to humans for 40 to 70 days, produced opiate withdrawal symptoms. Since addiction to diphenoxylate hydrochloride is possible at high doses, the recommended dosage should not be exceeded.

OVERDOSAGE

RECOMMENDED DOSAGE SCHEDULES SHOULD BE STRICTLY FOLLOWED. THIS MEDICATION SHOULD BE KEPT IN A CHILD-RESISTANT CONTAINER AND OUT OF THE REACH OF CHILDREN, SINCE AN OVERDOSAGE MAY RESULT IN SEVERE, EVEN FATAL, RESPIRATORY DEPRESSION.

Diagnosis: Initial signs of overdosage may include dryness of the skin and mucous membranes, mydriasis, restlessness, flushing, hyperthermia, and tachycardia followed by lethargy or coma, hypotonic reflexes, nystagmus, pinpoint pupils, and respiratory depression. Respiratory depression may be evidenced as late as 30 hours after ingestion and may recur despite an initial response to narcotic antagonists. TREAT ALL POSSIBLE LOMOTIL OVERDOSAGES AS SERIOUS AND MAINTAIN MEDICAL OBSERVATION FOR AT LEAST 48 HOURS, PREFERABLY UNDER CONTINUOUS HOSPITAL CARE.

Treatment: In the event of overdose, induction of vomiting, gastric lavage, establishment of a patent airway, and possibly mechanically assisted respiration are advised. In vitro and animal studies indicate that activated charcoal may significantly decrease the bioavailability of diphenoxylate. In noncomatose patients, a slurry of 100 g of activated charcoal can be administered immediately after the induction of vomiting or gastric lavage.

A pure narcotic antagonist (eg, naloxone) should be used in the treatment of respiratory depression caused by Lomotil. When a narcotic antagonist is administered intravenously, the onset of action is generally apparent within two minutes. It may also be administered subcutaneously or intramuscularly, providing a slightly less rapid onset of action but a more prolonged effect.

To counteract respiratory depression caused by Lomotil overdosage, the following dosage schedule for the narcotic antagonist naloxone hydrochloride should be followed:

Adult dosage: An initial dose of 0.4 mg to 2 mg of naloxone hydrochloride may be administered intravenously. If the desired degree of counteraction and improvement in respiratory functions is not obtained, it may be repeated at 2- to 3-minute intervals. If no response is observed after 10 mg of naloxone hydrochloride has been administered, the diagnosis of narcotic-induced or partial narcotic-induced toxicity should be questioned. Intramuscular or subcutaneous administration may be necessary if the intravenous route is not available.

Children: The usual initial dose in children is 0.01 mg/kg body weight given I.V. If this dose does not result in the desired degree of clinical improvement, a subsequent dose of 0.1 mg/kg body weight may be administered. If an I.V. route of administration is not available, naloxone hydrochloride may be administered I.M. or S.C. in divided doses. If necessary, naloxone hydrochloride can be diluted with sterile water for injection.

Following initial improvement of respiratory function, repeated doses of naloxone hydrochloride may be required to counteract recurrent respiratory depression. Supplemental intramuscular doses of naloxone hydrochloride may be utilized to produce a longer-lasting effect.

Since the duration of action of diphenoxylate hydrochloride is longer than that of naloxone hydrochloride, improvement of respiration following administration may be followed by recurrent respiratory depression. Consequently, continuous observation is necessary until the effect of diphenoxylate hydrochloride on respiration has passed. This effect may persist for many hours. The period of observation should extend over at least 48 hours, preferably under continuous hospital care. Although signs of overdosage and respiratory depression may not be evident soon after ingestion of diphenoxylate hydrochloride, respiratory depression may occur from 12 to 30 hours later.

DOSAGE AND ADMINISTRATION

DO NOT EXCEED RECOMMENDED DOSAGE.

Adults: The recommended initial dosage is two Lomotil tablets four times daily or 10 ml (two regular teaspoonfuls) of Lomotil liquid four times daily (20 mg per day). Most patients will require this dosage until initial control has been achieved, after which the dosage may be reduced to meet individual requirements. Control may often be maintained with as little as 5 mg (two tablets or 10 ml of liquid) daily.

Clinical improvement of acute diarrhea is usually observed within 48 hours. If clinical improvement of chronic diarrhea after treatment with a maximum daily dose of 20 mg of diphenoxylate hydrochloride is not observed within 10 days, symptoms are unlikely to be controlled by further administration.

Children: Lomotil is not recommended in children under 2 years of age and should be used with special caution in young children (see WARNINGS and PRECAUTIONS). The nutritional status and degree of dehydration must be considered. In children under 13 years of age, use Lomotil liquid. Do not use Lomotil tablets for this age group.

Only the plastic dropper should be used when measuring Lomotil liquid for administration to children.

Dosage schedule for children: The recommended initial total daily dosage of Lomotil liquid for children is 0.3 to 0.4 mg/kg, administered in four divided doses. The following table provides an approximate initial daily dosage recommendation for children.

Age
(years) Approximate weight Dosage in ml (four times daily) (kg) (lb)
2 11–14 24–31 1.5–3.0
3 12–16 26–35 2.0–3.0
4 14–20 31–44 2.0–4.0
5 16–23 35–51 2.5–4.5
6–8 17–32 38–71 2.5–5.0
9–12 23–55 51–121 3.5–5.0

These pediatric schedules are the best approximation of an average dose recommendation which may be adjusted downward according to the overall nutritional status and degree of dehydration encountered in the sick child. Reduction of dosage may be made as soon as initial control of symptoms has been achieved. Maintenance dosage may be as low as one-fourth of the initial daily dosage. If no response occurs within 48 hours, Lomotil is unlikely to be effective.

KEEP THIS AND ALL MEDICATIONS OUT OF THE REACH OF CHILDREN.

HOW SUPPLIED

Tablets—round, white, with SEARLE debossed on one side and 61 on the other side and containing 2.5 mg of diphenoxylate hydrochloride and 0.025 mg of atropine sulfate, supplied as:

NDC Number Size

0025-0061-31 bottle of 100

0025-0061-51 bottle of 500

0025-0061-52 bottle of 1,000

0025-0061-55 bottle of 2,500

0025-0061-34 carton of 100 unit dose

Liquid—containing 2.5 mg of diphenoxylate hydrochloride and 0.025 mg of atropine sulfate per 5 ml; bottles of 2 fl oz (NDC Number 0025-0066-02). Dispense only in original container.

A plastic dropper calibrated in increments of 1/2 ml (1/4 mg) with a capacity of 2 ml (1 mg) accompanies each 2-oz bottle of Lomotil liquid. Only this plastic dropper should be used when measuring Lomotil liquid for administration to children.

SPL UNCLASSIFIED SECTION

Rx only

[Logo]

LAB-0065-2.0

October 2005